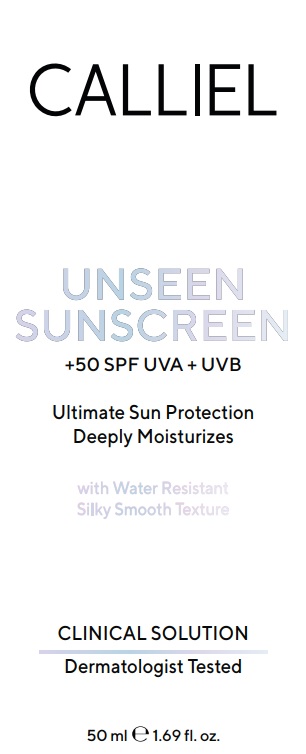 DRUG LABEL: CALLIEL UNSEEN SUNSCREEN SPF 50
NDC: 87411-0006 | Form: CREAM
Manufacturer: CALLIEL PHARMA KOZMETIK SANAYI VE TICARET ANONIM SIRKETI
Category: otc | Type: HUMAN OTC DRUG LABEL
Date: 20260207

ACTIVE INGREDIENTS: ETHYLHEXYL METHOXYCINNAMATE 8 g/100 g; OCTOCRYLENE 5 g/100 g; BUTYL METHOXYDIBENZOYLMETHANE 4.6 g/100 g; HOMOSALATE 4.6 g/100 g
INACTIVE INGREDIENTS: GLYCERYL STEARATE 1.55 g/100 g; ETHYLHEXYLGLYCERIN 0.05 g/100 g; SILICA 2.2 g/100 g; CETEARETH-20 1.7 g/100 g; CETEARYL ALCOHOL 5 g/100 g; AQUA 46.08 g/100 g; DIMETHICONE/VINYL DIMETHICONE CROSSPOLYMER (SOFT PARTICLE) 8 g/100 g; PHENOXYETHANOL 0.82 g/100 g; DIMETHICONE 12.4 g/100 g

Active ingredients

Ethylhexyl Methoxycinnamate 8%
Octocrylene 5%
Butyl Methoxydibenzoylmethane 4.6%
Homosalate 4.6%

Uses

• helps prevent sunburn
• if used as directed with other sun protection measures (see Directions), decreases the risk of skin cancer and early skin aging caused by the sun

Do not use on damaged or broken skin

Stop use and ask a doctor if rash occurs.

Keep out of reach of children. If swallowed, get medical help or contact a Poison Control Center right away.

Directions

• apply liberally 15 minutes before sun exposure
• reapply:
• after 80 minutes of swimming or sweating
• immediately after towel drying
• at least every 2 hours
• children under 6 months: Ask a doctor

Sun Protection Measures: Spending time in the sun increases your risk of skin cancer and early skin aging caused by the sun. To decrease this risk, regularly use a sunscreen with a Broad Spectrum SPF 15 or higher and other sun protection measures including:
• limit time in the sun, especially from 10 a.m. – 2 p.m.
• wear long-sleeve shirts, pants, hats, and sunglasses

Warnings

For external use only

Purpose

Sunscreen

Inactive ingredients

Aqua, Dimethicone/Vinyl Dimethicone Crosspolymer, Dimethicone, Cetearyl Alcohol, Ceteareth-20, Glyceryl Stearate, Silica, Phenoxyethanol, Ethylhexylglycerin.

PACKAGE LABEL

CALLIEL

UNSEEN SUNSCREEN

SPF 50+
UVA + UVB

Ultimate Sun Protection
Deeply Moisturizes

Water Resistant
Silky Smooth Texture

50 mL (1.69 fl oz)